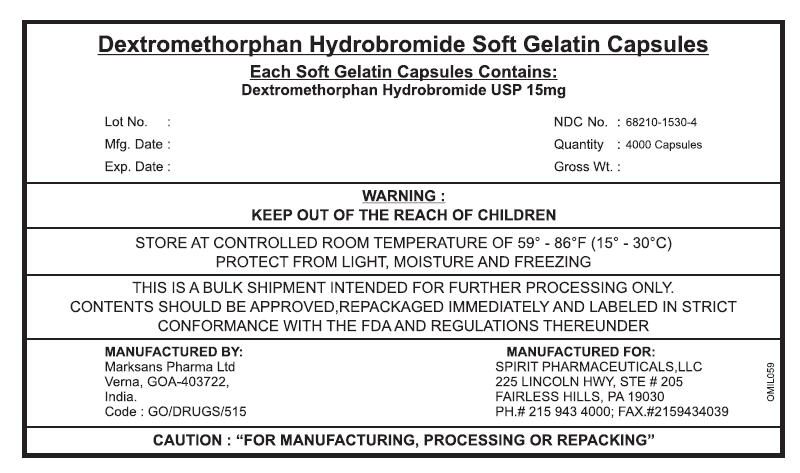 DRUG LABEL: DEXTROMETHORPHAN HYDROBROMIDE
NDC: 68210-1530 | Form: CAPSULE, LIQUID FILLED
Manufacturer: SPIRIT PHARMACEUTICALS,LLC
Category: otc | Type: HUMAN OTC DRUG LABEL
Date: 20100726

ACTIVE INGREDIENTS: DEXTROMETHORPHAN HYDROBROMIDE 15 mg/1 1
INACTIVE INGREDIENTS: POLYETHYLENE GLYCOL 400; PROPYLENE GLYCOL; GELATIN; POVIDONE; SORBITOL; WATER; GLYCERIN; FD&C RED NO. 40; FD&C BLUE NO. 1

Dextrmethorphan Hydrobromide Soft Gelatin Capsules

Drug Facts

Active ingredients (in each LiquiCap)

Dextromethorphan Hbr 15 mg

Purpose

Cough Suppressant

Uses temporarily

relieves cough due to minor throat and bronchial irritation may occur with a cold

Warnings

Do not use

- if you are now taking a prescription monoamine oxidase inhibitor(MAOI) (certain drugs for depression, psychiatric or emotional conditions, or Parkinson's disease), or for 2 weeks after stopping the MAOI drug. If you do not know if your prescription drug contains an MAOI, ask a doctor or pharmacist before taking this product.

Ask a doctor before use if you have

- a cough that occurs with too much phlegm(mucus)
- a cough that lasts or is chronic cough as occurs with smoking, asthma or emphysema

Stop use and ask doctor if

- cough lasts for more than 7 days,comes back or is accompanied by fever, rash, or persistent headache

These could be signs of a serious conditions

PREGNANCY OR BREAST FEEDING

If pregnant or breast-feeding, ask a health professional before use

Keep out of reach of children.

Overdose Warning

In case of overdose,get medical help or contact a poison control center right away.

Direction

- do not take more than 8 liquidgels in any 24 hour period.
- adults and children 12 years over : take 2 liquidgels every 6 to 8 hours, as needed
- Children under 12years: ask a doctor

Other information

- each tablet contains : Store at room temperature

Inactive ingredients

FD &C Red No 40 IH, Polyethylene Glycol , Gelatin, Glycerin, Povidone, Purified water, Sorbitol

PRINCIPAL DISPLAY PANEL - 15mg Tablet Shipper Label

Dextromethorphan Hydrobromide Soft Gelatin Capsules
Each Soft Gelatin Capsules Contains:
Dextromethorphan Hydrobromide USP 15mg

Lot No. :

Mfg. Date :

Exp. Date :

NDC No. : 68210-1530-4

Quantity : 4000 Capsules

Gross Wt. :

WARNING :
KEEP OUT OF THE REACH OF CHILDREN

STORE AT CONTROLLED ROOM TEMPERATURE OF 59° - 86°F (15° - 30°C)
PROTECT FROM LIGHT, MOISTURE AND FREEZING

THIS IS A BULK SHIPMENT INTENDED FOR FURTHER PROCESSING ONLY.
CONTENTS SHOULD BE APPROVED,REPACKAGED IMMEDIATELY AND LABELED IN STRICT
CONFORMANCE WITH THE FDAAND REGULATIONS THEREUNDER

MANUFACTURED BY:
Marksans Pharma Ltd
Verna, GOA-403722,
India.
Code : GO/DRUGS/515

MANUFACTURED FOR:
SPIRIT PHARMACEUTICALS,LLC
225 LINCOLN HWY, STE # 205
FAIRLESS HILLS, PA 19030
PH.# 215 943 4000; FAX.#2159434039

OMIL059

CAUTION : "FOR MANUFACTURING, PROCESSING OR REPACKING"